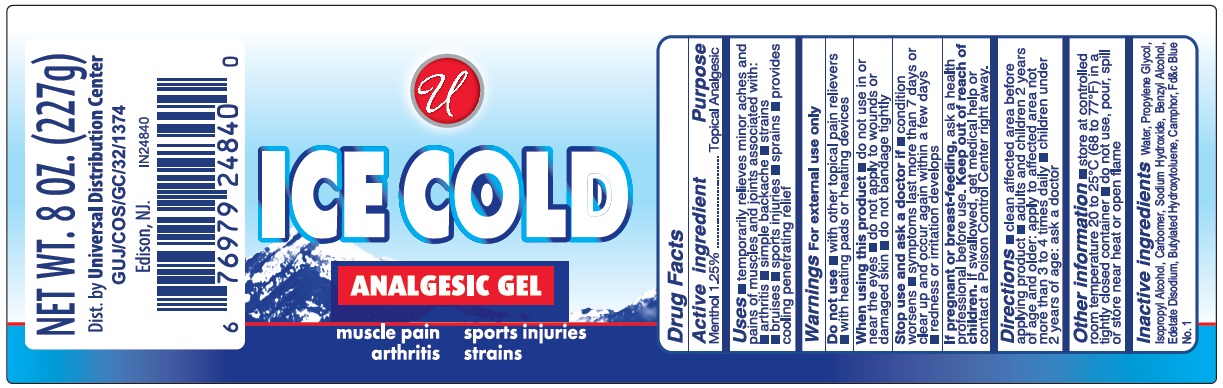 DRUG LABEL: Universal Ice Cold Analgesic
NDC: 52000-105 | Form: GEL
Manufacturer: Universal Distribution Center LLC
Category: otc | Type: HUMAN OTC DRUG LABEL
Date: 20231115

ACTIVE INGREDIENTS: MENTHOL, UNSPECIFIED FORM 1.25 g/100 g
INACTIVE INGREDIENTS: CAMPHOR (SYNTHETIC); BENZYL ALCOHOL; BUTYLATED HYDROXYTOLUENE; CARBOMER HOMOPOLYMER TYPE C (ALLYL PENTAERYTHRITOL CROSSLINKED); FD&C BLUE NO. 1; EDETATE DISODIUM; ISOPROPYL ALCOHOL; PROPYLENE GLYCOL; SODIUM HYDROXIDE; WATER

UNIVERSAL ICE COLD ANALGESIC GEL

Active Ingredients

Menthol 1.25%

Purpose

Topical Analgesic

Uses

Temporary relieves of minor aches and pains in muscles and joints associated with

- arthritis
- simple backache
- strains
- bruises
- sports injuries
- sprains
- provides cooling penetrating relief

Warnings

For external use only

Do not use

- with other topical pain relievers
- with heating pads or heating devices

When using this product

- do not use in or near the eyes
- do not apply to wounds or damaged skin
- do not bandage tightly

Stop use and ask doctor if

- condition worsens
- symptoms last more than 7 days or clean up and occur again within a few days
- redness or irritation develops

If pregnant or breast-feeding,

- ask a health professional before use

Keep out of the reach of children

If swallowed, get medical help or contact a Poison Control Center right away

Directions

- clean affected area before applying product
- adults and children 2 years of age and older: apply to affected area not more than 3 to 4 times daily
- children under 2 years of age: ask a doctor

Other information

- store at controlled room temperature 20 to 25oC (68 to 77oF in a tightly closed container
- do not use, pour, spill or store near heat or open flame

Inactive ingredients

Water, Propylene glycol, Isopropyl alcohol, Carbomer, Sodium hydroxide, Benzyl alcohol, Edetate Disodium, Butylated hydroxytoluene, Camphor, Fd&c Blue No. 1

PRINCIPAL DISPLAY PANEL

ICE COLD
ANALGESIC GEL
8 FL.OZ (227 GRAM)